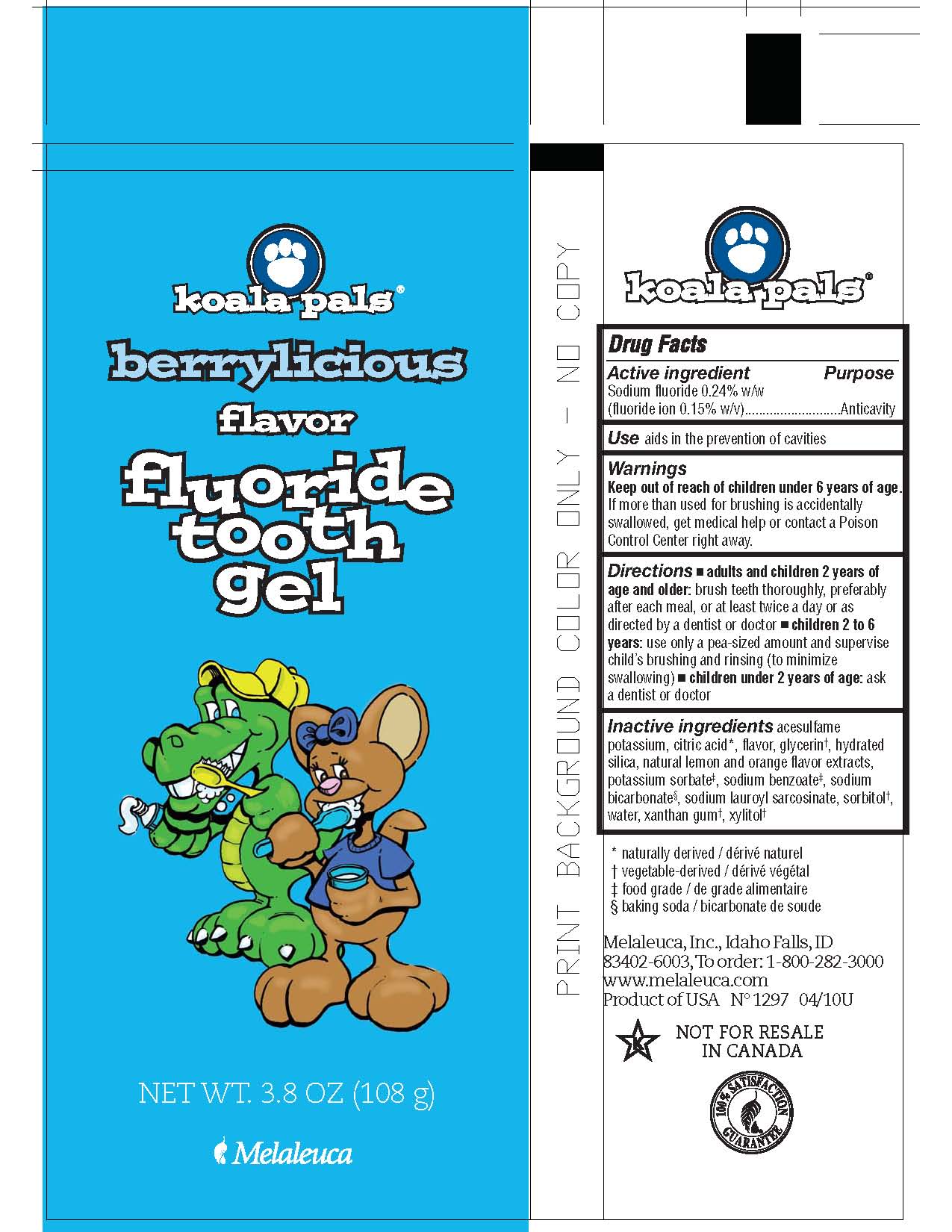 DRUG LABEL: Koala Pals
NDC: 54473-300 | Form: PASTE, DENTIFRICE
Manufacturer: Melaleuca, Inc.
Category: otc | Type: HUMAN OTC DRUG LABEL
Date: 20251231

ACTIVE INGREDIENTS: SODIUM FLUORIDE 0.2592 g/108 g
INACTIVE INGREDIENTS: ANHYDROUS CITRIC ACID; ACESULFAME POTASSIUM; GLYCERIN; HYDRATED SILICA; POTASSIUM SORBATE; SODIUM BENZOATE; SODIUM BICARBONATE; SODIUM LAUROYL SARCOSINATE; SORBITOL; WATER; XANTHAN GUM; XYLITOL

Koala Pals Tooth Gel +Fluoride Berrylicious

Active ingredient
Sodium Fluoride 0.24% (fluoride ion 0.15% w/v)

Purpose
Anticavity

INDICATIONS AND USAGE

Use aids in the prevention of cavities

Warnings
Keep out of reach of children under 6 years of age. If more than used for brushing is accidentally swallowed, get medical help or contact a Poison Control Center right away.

Directions

- adults and children 2 years of age and older: brush teeth thoroughly, preferably after each meal, or at least twice a day or as directed by a dentist or doctor
- children 2 to 6 years: use only a pea-sized amount and supervise child's brushing and rinsing (to minimize swallowing)
- children under 2 years of age: ask a dentist or doctor

INACTIVE INGREDIENT

Inactive ingredients acesulfame potassium, citric acid, flavor, glycerin, hydrated silica, natural lemon and orange flavor extracts, potassium sorbate, sodium benzoate, sodium bicarbonate, sodium lauroyl sarcosinate, sorbitol, water, xanthan gum, xylitol

Warnings